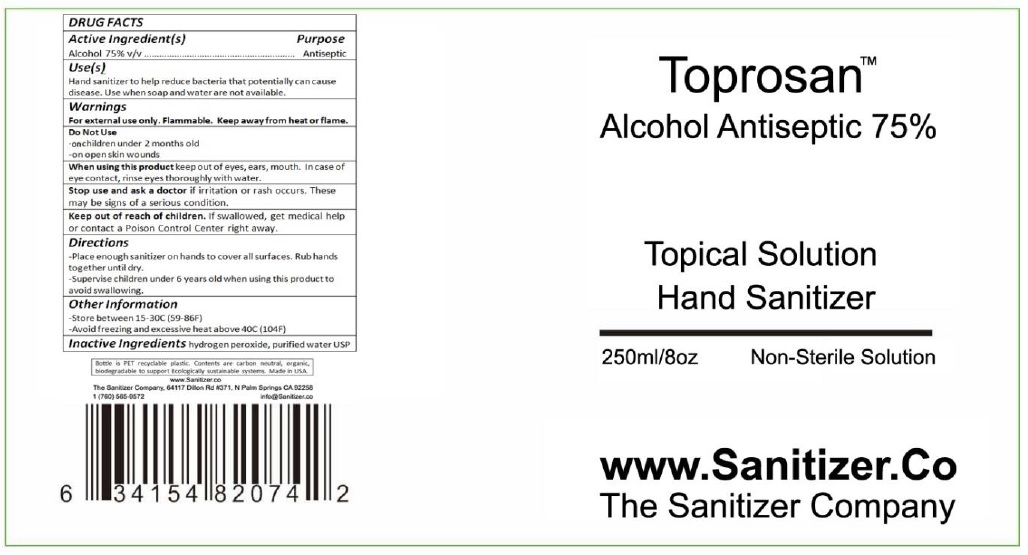 DRUG LABEL: Toprosan hand sanitizer
NDC: 80149-001 | Form: LIQUID
Manufacturer: Toprosan-Valuerays
Category: otc | Type: HUMAN OTC DRUG LABEL
Date: 20200818

ACTIVE INGREDIENTS: ALCOHOL 75 mL/100 mL
INACTIVE INGREDIENTS: WATER; HYDROGEN PEROXIDE

Active Ingredient

Alcohol 75% v/v.

Purpose

Antiseptic

Uses

Hand sanitizer to help reduce bacteria that potentially can cause disease. Use when soap and water are not available.

Warnings

For external use only. Flammable. Keep away from heat or flame.

Do Not Use

on children under 2 months old

or on open skin wounds.

When using this product keep out of eyes, ears, mouth. In case of eye contact, rinse eyes thoroughly with water.

Stop use and ask a doctor if irritation or rash occurs. These may be signs of a serious condition.

Keep out of reach of children. If swallowed, get medical help or contact a Poison Control Center right away.

Directions

Place enough sanitizer on hands to cover all surfaces. Rub hands together until dry.
Supervise children under 6 years old when using this product to avoid swallowing.

Inactive ingredients

Hydrogen peroxide, USP purified water.